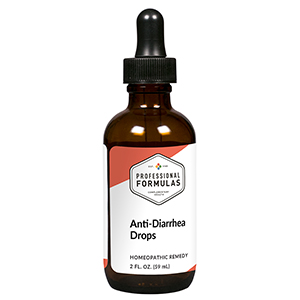 DRUG LABEL: Anti-Diarrhea Drops
NDC: 63083-2003 | Form: LIQUID
Manufacturer: Professional Complementary Health Formulas
Category: homeopathic | Type: HUMAN OTC DRUG LABEL
Date: 20190815

ACTIVE INGREDIENTS: ALOE 4 [hp_X]/59 mL; RHEUM OFFICINALE STEM 4 [hp_X]/59 mL; CINCHONA OFFICINALIS BARK 6 [hp_X]/59 mL; CITRULLUS COLOCYNTHIS FRUIT PULP 6 [hp_X]/59 mL; PODOPHYLLUM 6 [hp_X]/59 mL; TOXICODENDRON PUBESCENS LEAF 6 [hp_X]/59 mL; VERATRUM ALBUM ROOT 6 [hp_X]/59 mL; ARSENIC TRIOXIDE 8 [hp_X]/59 mL; MERCURIC CHLORIDE 12 [hp_X]/59 mL
INACTIVE INGREDIENTS: ALCOHOL; WATER

C3

ACTIVE INGREDIENTS

Aloe socotrina 4X
Rheum officinale 4X
Cinchona officinalis 6X
Colocynthis 6X
Podophyllum peltatum 6X
Rhus toxicodendron 6X
Veratrum album 6X
Arsenicum album 8X
Mercurius corrosivus 12X

QUESTIONS

Professional Formulas

PO Box 2034 Lake Oswego, OR 97035

INDICATIONS

For the temporary relief of occasional diarrhea or flatulence.*

PURPOSE

*Claims based on traditional homeopathic practice, not accepted medical evidence. Not FDA evaluated.

WARNINGS

Do not use for more than 30 days. Consult a doctor if condition worsens or if symptoms persist. Keep out of the reach of children. In case of overdose, get medical help or contact a poison control center right away. If pregnant or breastfeeding, ask a healthcare professional before use.

Keep out of the reach of children.

PREGNANCY OR BREAST FEEDING

If pregnant or breastfeeding, ask a healthcare professional before use.

DIRECTIONS

Place drops under tongue 30 minutes before/after meals. Adults and children 12 years and over: Take 10 drops up to 3 times per day for up to 6 weeks. For immediate onset of symptoms, take 10 to 15 drops every 15 minutes up to 3 hours. For less severe symptoms, take 10-15 drops hourly up to 8 hours. Consult a physician for use in children under 12 years of age.

OTHER INFORMATION

Tamper resistant. If seal is broken, do not use. After opening, close container tightly and store at room temperature away from heat.

INACTIVE INGREDIENTS

20% ethanol, purified water.

LABEL

Est 1985

Professional Formulas

Complementary Health

Anti-Diarrhea Drops

Homeopathic Remedy

2 FL. OZ. (59 mL)